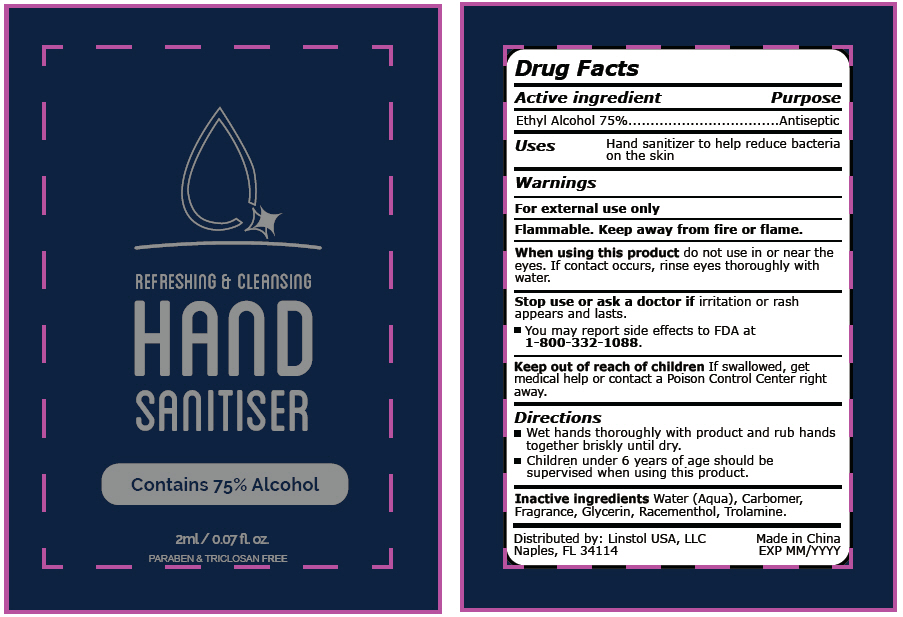 DRUG LABEL: Linstol Refreshing and Cleansing Hand Sanitizer
NDC: 76982-3864 | Form: GEL
Manufacturer: Linstol USA, LLC
Category: otc | Type: HUMAN OTC DRUG LABEL
Date: 20221221

ACTIVE INGREDIENTS: ALCOHOL 75 mL/100 mL
INACTIVE INGREDIENTS: GLYCERIN; RACEMENTHOL; TROLAMINE; WATER; CARBOMER HOMOPOLYMER, UNSPECIFIED TYPE

Linstol Refreshing & Cleaning Hand Sanitizer

Drug Facts

Active ingredient

Ethyl Alcohol 75%

Purpose

Antiseptic

Uses

Hand sanitizer to help reduce bacteria on the skin

Warnings

For external use only

Flammable. Keep away from fire or flame.

When using this product do not use in or near the eyes. If contact occurs, rinse eyes thoroughly with water.

Stop use or ask a doctor if irritation or rash appears and lasts.

- You may report side effects to FDA at 1-800-FDA-1088.

Keep out of reach of children If swallowed, get medical help or contact a Poison Control Center right away.

Directions

- Wet hands thoroughly with product and rub hands together briskly until dry.
- Children under 6 years of age should be supervised when using this product.

Inactive ingredients

Water (Aqua), Carbomer, Fragrance, Glycerin, Racementhol, Trolamine.

Distributed by: Linstol USA, LLC
Naples, FL 34114

PRINCIPAL DISPLAY PANEL - 2 ml Packet

REFRESHING & CLEANSING

HAND
SANITISER

Contains 75% Alcohol

2ml / 0.07 fl. oz.
PARABEN & TRICLOSAN FREE